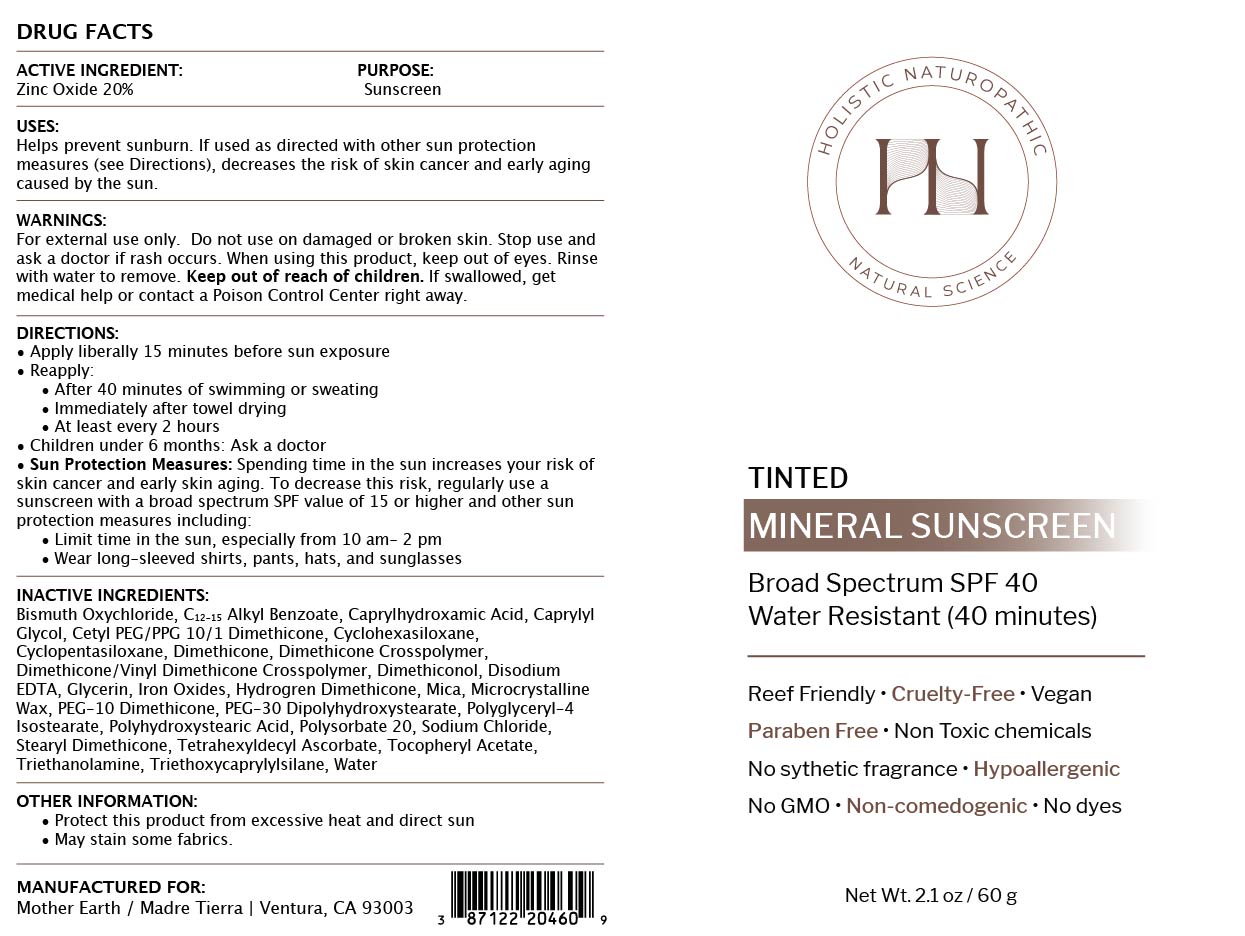 DRUG LABEL: Tinted Mineral Sunscreen
NDC: 87122-204 | Form: CREAM
Manufacturer: MADRE TIERRA, INC.
Category: otc | Type: HUMAN OTC DRUG LABEL
Date: 20251216

ACTIVE INGREDIENTS: ZINC OXIDE 200 mg/1 g
INACTIVE INGREDIENTS: DIMETHICONOL (2000 CST); MICA; CETYL PEG/PPG-10/1 DIMETHICONE (HLB 4); CYCLOPENTASILOXANE; SODIUM CHLORIDE; TRIETHOXYCAPRYLYLSILANE; C12-15 ALKYL BENZOATE; CYCLOHEXASILOXANE; POLYSORBATE 20; EDETATE DISODIUM ANHYDROUS; DIMETHICONE; CI 77492; TETRAHEXYLDECYL ASCORBATE; MICROCRYSTALLINE WAX; POLYGLYCERYL-4 ISOSTEARATE; GLYCERIN; BISMUTH OXYCHLORIDE; DIMETHICONE/VINYL DIMETHICONE CROSSPOLYMER (SOFT PARTICLE); HYDROGEN DIMETHICONE (20 CST); PEG-10 DIMETHICONE (600 CST); CAPRYLYL GLYCOL; DIMETHICONE CROSSPOLYMER; CI 77499; ALPHA-TOCOPHEROL ACETATE; POLYHYDROXYSTEARIC ACID (2300 MW); CAPRYLHYDROXAMIC ACID; PEG-30 DIPOLYHYDROXYSTEARATE; STEARYL DIMETHICONE (400 MPA.S AT 50C); TRIETHANOLAMINE; WATER; CI 77491

Active Ingredients:

Zinc Oxide 20%

Purpose:

Sunscreen

Uses:

Helps Prevent Sunburn. If used as directed with other sun protection measures (see “Directions”), decreases the risk of skin cancer and early skin aging caused by the sun.

Warnings:

For external use only. Do not use on broken or damaged skin. Stop use and ask a doctor if rash occurs. When using this product, keep out of eyes. Rinse with water to remove. Keep out of reach of children. If swallowed, get medical help or contact a poison control center right away.

Warnings:

Keep out of reach of children

Directions:

Apply liberally 15 minutes before sun exposure. Use a water-resistant product if swimming or sweating. Reapply at least every 2 hours. Children under 6 months: Ask a doctor. Sun Protection Measures: Spending time in the sun increases your risk of skin cancer and early skin aging. To decrease this risk, regularly use a sunscreen with a Broad-Spectrum SPF value of 15 or higher and other sun protection measures including: Limit time in the sun, especially from 10 a.m. - 2 p.m. Wear long-sleeved shirts, pants, hats and sunglasses.

Inactive Ingredients:

Bismuth Oxychloride, C12-15 Alkyl Benzoate, Caprylhydroxamic Acid, Caprylyl Glycol, Cetyl PEG/PPG-10/1 Dimethicone, Cyclohexasiloxane, Cyclopentasiloxane, Dimethicone, Dimethicone Crosspolymer, Dimethicone/Vinyl Dimethicone Crosspolymer, Dimethiconol, Disodium EDTA, Glycerin, Hydrogen Dimethicone, Iron Oxides, Mica, Microcrystalline Wax, PEG-10 Dimethicone, PEG-30 Dipolyhydroxystearate, Polyglyceryl-4 Isostearate, Polyhydroxystearic Acid, Polysorbate 20, Sodium Chloride, Stearyl Dimethicone, Tetrahexyldecyl Ascorbate, Tocopheryl Acetate, Triethanolamine, Triethoxycaprylylsilane, Water

Other Information:

- Protect this product from excessive heat and direct sun
- May Stain Some fabrics